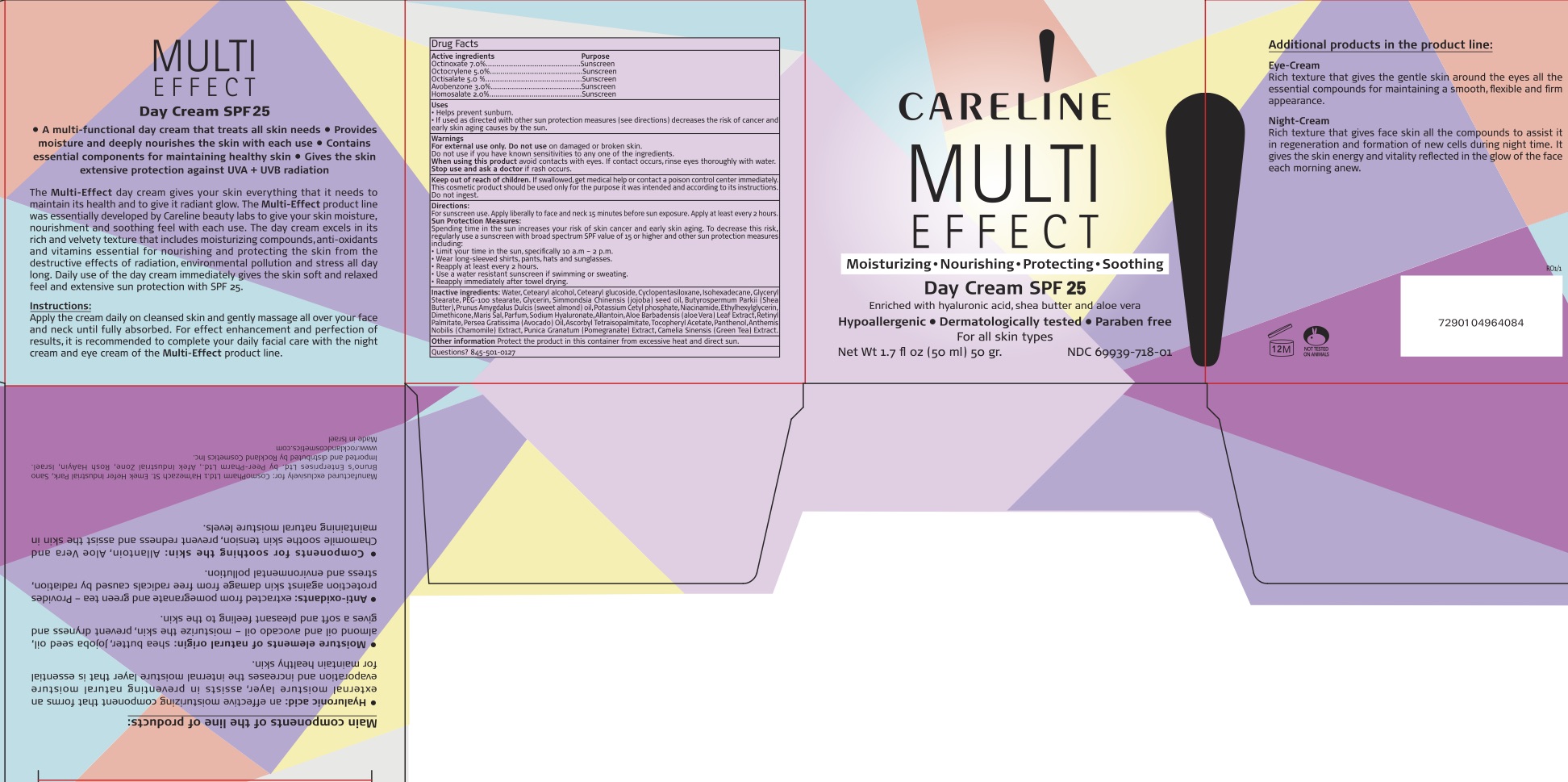 DRUG LABEL: Multi Effect Day Cream SPF 25
NDC: 69435-1701 | Form: CREAM
Manufacturer: Sano International Ltd.
Category: otc | Type: HUMAN OTC DRUG LABEL
Date: 20171116

ACTIVE INGREDIENTS: OCTOCRYLENE 5 g/100 mL; OCTISALATE 5 g/100 mL; AVOBENZONE 3 g/100 mL; HOMOSALATE 2 g/100 mL; OCTINOXATE 7 g/100 mL
INACTIVE INGREDIENTS: JOJOBA OIL; PHENOXYETHANOL; GLYCERYL MONOSTEARATE; ETHYLHEXYLGLYCERIN; ALMOND OIL; DMDM HYDANTOIN; ALLANTOIN; CHLORPHENESIN; HYALURONATE SODIUM; ASCORBYL TETRAISOPALMITATE; ISOHEXADECANE; CETOSTEARYL ALCOHOL; CETEARYL GLUCOSIDE; CYCLOMETHICONE 5; GLYCERIN; PUNICA GRANATUM ROOT BARK; SHEA BUTTER; POTASSIUM CETYL PHOSPHATE; NIACINAMIDE; DIMETHICONE; SEA SALT; ALOE VERA LEAF; VITAMIN A PALMITATE; .ALPHA.-TOCOPHEROL ACETATE; PANTHENOL; GREEN TEA LEAF; CHAMAEMELUM NOBILE FLOWER; AVOCADO OIL; WATER; DIETHYLAMINO HYDROXYBENZOYL HEXYL BENZOATE

Multi Effect Day Cream SPF 25

PACKAGE LABEL

ACTIVE INGREDIENT

Octinoxate 7%

Octocrylene 5%

Octisalate 5%

Avobenzone 3%

Homosalate 2%

Keep out of reach of children.

PURPOSE

Provides SPF 25 protection

INDICATIONS AND USAGE

To Use: Smooth onto face.
For Sunscreen Use: Apply liberally 15 minutes before sun exposure. Reapply at least every 2 hours.
Sun Protection Measures: Spending time in the sun increases your risk of skin cancer and early skin aging. To decrease this risk, regularly use a sunscreen with a broad spectrum SPF of 15 or higher and other sun protection measures including: Limit time in the sun, especially from 10 a.m. - 2 p.m. Wear long-sleeve shirts, pants, hats, and sunglasses.

DOSAGE AND ADMINISTRATION

Smooth on to face.